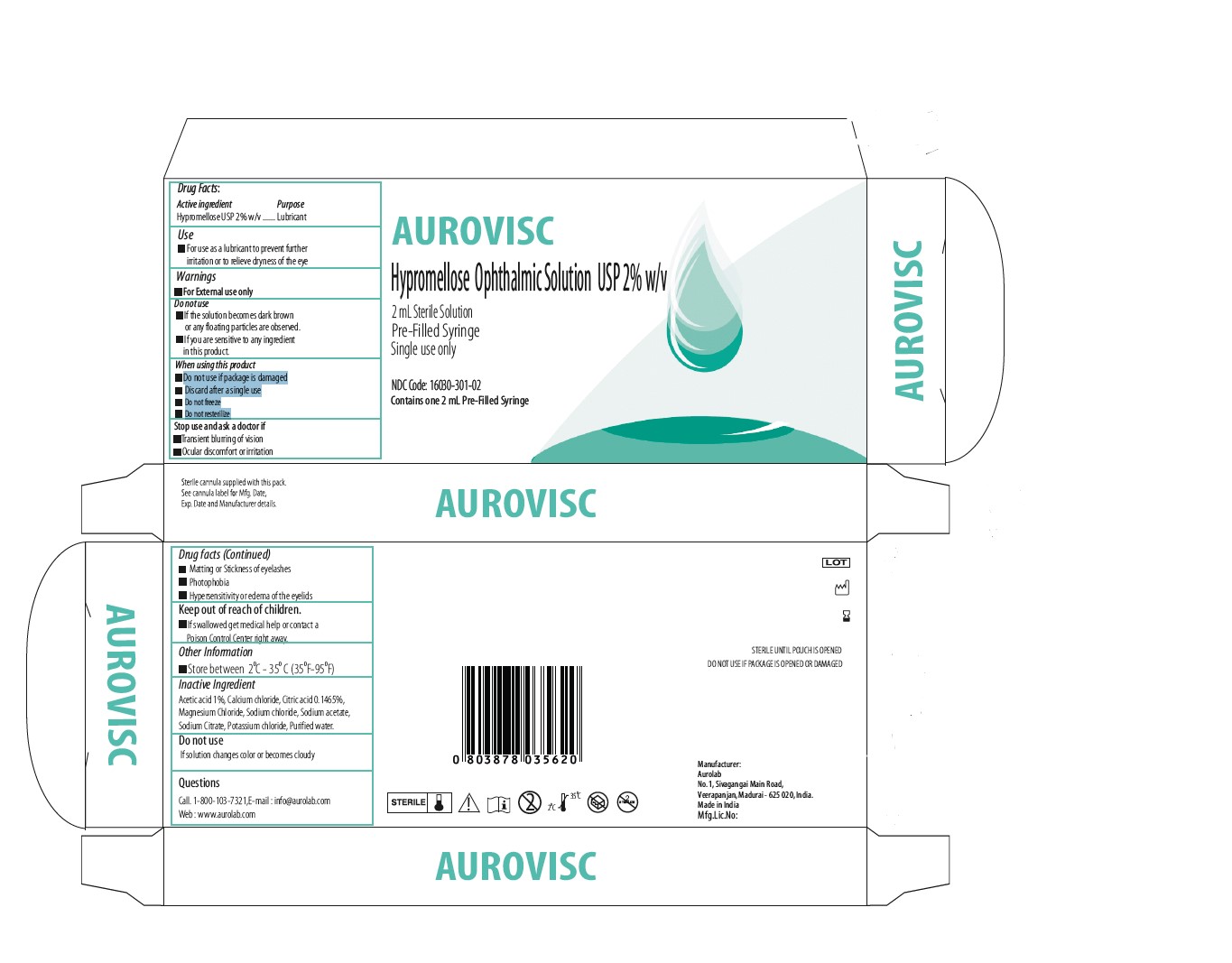 DRUG LABEL: Aurovisc Lubricant HYPROMELLOSE 2208 (15000 MPA.S) Gel/Drops
NDC: 16030-303 | Form: SOLUTION, GEL FORMING / DROPS
Manufacturer: Aurolab
Category: otc | Type: HUMAN OTC DRUG LABEL
Date: 20260127

ACTIVE INGREDIENTS: HYPROMELLOSE 2208 (15000 MPA.S) 20 mg/1 mL
INACTIVE INGREDIENTS: SODIUM CITRATE; SODIUM ACETATE; POTASSIUM CHLORIDE; WATER; SODIUM CHLORIDE; MAGNESIUM CHLORIDE; CALCIUM CHLORIDE; CITRIC ACID ACETATE; ACETIC ACID

ACTIVE INGREDIENT

Hypromellose USP 2% w/v

INACTIVE INGREDIENT

1. Acetic acid 1%
2. Calcium chloride
3. Citric acid 0.1465%
4. Magnesium Chloride
5. Sodium chloride
6. Sodium acetate,
7. Sodium Citrate
8. Potassium chloride
9. Purified water.

USE

For use as a lubricant to prevent further irritation or to relieve dryness of the eye

QUESTIONS

Call. 1-800-103-7321,

E-mail : info@aurolab.com
Web : www.aurolab.com

KEEP OUT OF REACH OF CHILDREN

If swallowed get medical help or contact a Poison Control Center right away.

STOP USE

1. Transient blurring of vision
2. Ocular discomfort or irritation
3. Matting or Stickness of eyelashes
4. Photophobia
5. Hypersensitivity or edema of the eyelids

DO NOT USE

1. If the solution becomes dark brown or any floating particles are observed.
2. If you are sensitive to any ingredient in this product

WARNINGS

For External use only

INDIACATIONS AND USAGE

Do not use if package is damaged
Discard after a single use
Do not freeze
Do not resterilize

Purpose

Lubricant

Dose

Instill 1 or 2 drops in the affected eyes as needed